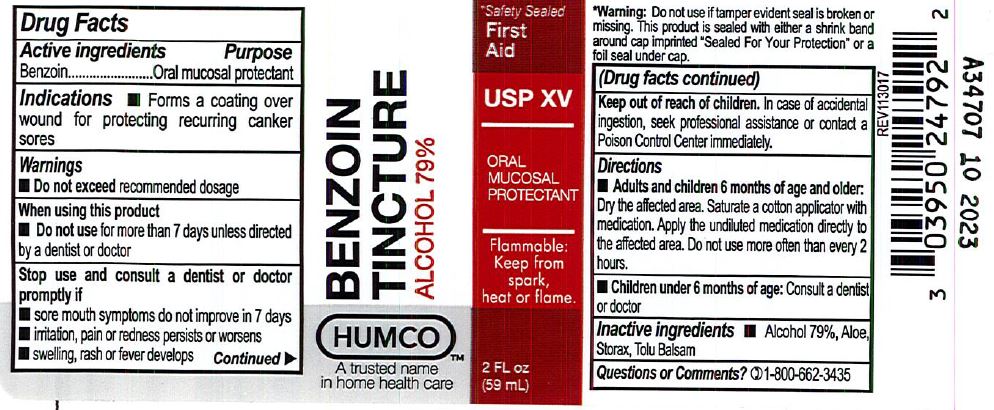 DRUG LABEL: Benzoin Tincture
NDC: 0395-0247 | Form: LIQUID
Manufacturer: Humco Holding Group, Inc.
Category: otc | Type: HUMAN OTC DRUG LABEL
Date: 20231215

ACTIVE INGREDIENTS: BENZOIN RESIN 1000 mg/1 mL
INACTIVE INGREDIENTS: ALCOHOL; ALOE; TOLU BALSAM

Humco Benzoin Tincture, NF

Drug Facts

Active Ingredient

Benzoin

Purpose

Oral mucosal protectant

Use

Forms a coating over wound for protecting recurring canker sores

Warnings

For externl use only. Do not swallow. Do not exceed recommended dosage.

When using this product

Children under 12 years of age should be supervised in the use of this product.

Do not use more than 7 days unless directed by a dentist or doctor.

Stop use and consult a dentist or doctor if

- sore mouth symptoms do not improve in 7 days.
- irritation, pain or redness persists or worsens.
- swelling, rash or fever develops.

Keep out of the reach of children.

In case of accidental ingestion, seek professional assistance or contact a Poison Control Center immeditely.

Directions

Adult and children 6 months of age and older: Dry the affected area, with cotton swab, apply undiluted to the affected area not more than every 2 hours.

Children under 6 months of age: Consult a dentist or doctor.

Inactive Ingredients

Alcohol 77%, Aloe, Stoax, tolu Balsam.

Questions or Comments?

1-800-662-3435